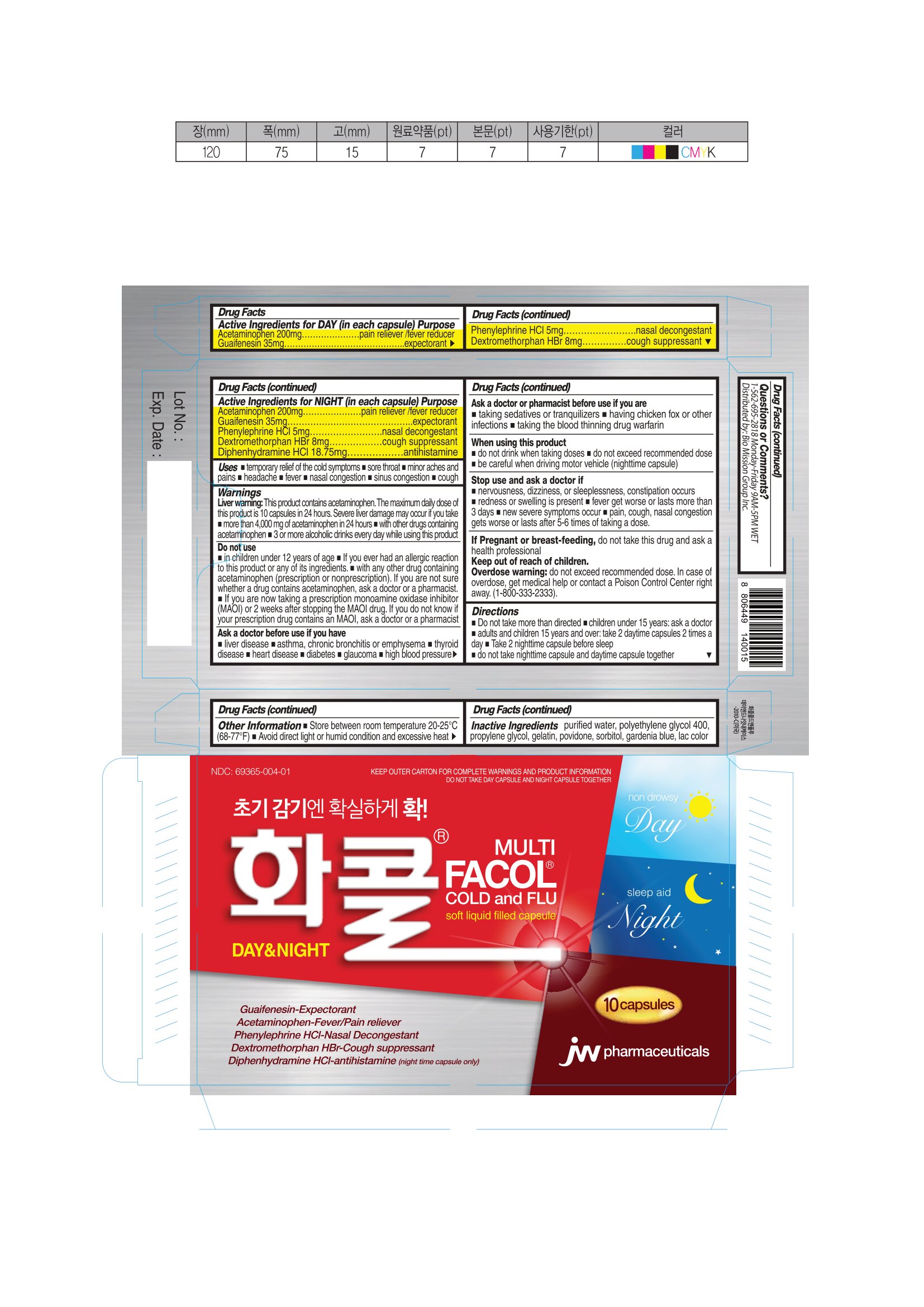 DRUG LABEL: Facol Cold and Flu Day and Night
NDC: 69365-004 | Form: CAPSULE, LIQUID FILLED
Manufacturer: JW HOLDINGS
Category: otc | Type: HUMAN OTC DRUG LABEL
Date: 20240828

ACTIVE INGREDIENTS: DIPHENHYDRAMINE HYDROCHLORIDE 18.75 mg/1 1; DEXTROMETHORPHAN HYDROBROMIDE 8 mg/1 1; PHENYLEPHRINE HYDROCHLORIDE 5 mg/1 1; GUAIFENESIN 35 mg/1 1; ACETAMINOPHEN 200 mg/1 1
INACTIVE INGREDIENTS: GELATIN 206.22 mg/1 1; POVIDONE K29/32 33 mg/1 1; PROPYLENE GLYCOL 40 mg/1 1; WATER 70.4 mg/1 1; SORBITOL 142.88 mg/1 1; POLYETHYLENE GLYCOL 400 440.25 mg/1 1; ALUMINUM OXIDE 2.185 mg/1 1; COCHINEAL 2.185 mg/1 1; GARDENIAN BLUE 0.49 1/1 1

FACOL COLD AND FLU DAY AND NIGHT

Active Ingredients for DAY (In each capsule).......Purpose Active Ingredients for NIGHT (In each capsule).......Purpose

Acetaminophen 200mg............................pain reliever/fever reducer

Guaifenesin 35mg....................................expectorant

phenylephrine HCl 5mg............................nasal decongestant

dextromethorphan Hbr8mg.......................cough suppressant

Acetaminophen 200mg............................pain reliever/fever reducer

Guaifenesin 35mg....................................expectorant

phenylephrine HCl 5mg............................nasal decongestant

dextromethorphan Hbr8mg.......................cough suppressant

Diphenhyddramine Hydrochloride 18.75mg......antihistamine

Uses

■ temporary relief of the following cold symptoms ■ sore throat ■ minor aches and pains ■ headache ■ fever ■ nasal congestion ■ sinus congestion ■ cough

Warnings

Liver warning: This product contains acetaminophen. The maximum daily dose of this product is 10 caplets in 24 hours. Severe liver damage may occur if you take
■ more than 4,000 mg of acetaminophen in 24 hours
■ with other drugs containing acetaminophen
■ 3 or more alcoholic drinks every day while using this product

Do not use

■ in children under 12 years of age
■ If you ever had an allergic reaction to this product or any of its ingredients.
■ with any other drug containing acetaminophen (prescription or nonprescription). If you are not sure whether a drug contains acetaminophen, ask a doctor or a pharmacist.
■ If you are now taking a prescription monoamine oxidase inhibitor (MAOI) or 2 weeks after stopping the MAOI drug. If you do not know if your prescription drug contains an MAOI, ask a doctor or a pharmacist

Ask a doctor before use if you have

■ liver disease ■asthma, chronic bronchitis or emphysema ■ thyroid disease ■ heart disease ■ diabetes ■ glaucoma ■ high blood pressure

Ask a doctor or pharmacist before use if you are

■ taking sedatives or tranquilizers ■ having chicken fox or other infections
■ taking the blood thinning drug warfarin

When using this product

■ Do not drink when taking doses ■Do not exceed recommended dose
■ be careful when driving motor vehicle (nighttime capsule)

Stop use and ask a doctor if

■ nervousness, dizziness, or sleeplessness, constipation occurs
■ redness or swelling is present ■ fever get worse or lasts more than 3 days
■ new severe symptoms occur ■ pain, cough, nasal congestion gets worse or lasts after 5-6 times of taking a dose

If Pregnant or breast-feeding

do not take this drug and ask a health professional

Overdose warning

Do not exceed recommended dose. In case of overdose, get medical help or contact a Poison Control Center right away. (1-800-333-2333).

Other Information

■ Store between room temperature 20-25°C (68-77°F)
■ Avoid direct light or humid condition and excessive heat

Inactive Ingredients

purified water, polyethylene glycol 400, propylene glycol, gelatin, povidone, sorbitol, gardenia blue, lac color

Questions or Comments?

1-562-695-2818 Monday - Friday 9AM-5PM WET

Distributed by: Bio Mission Group Inc.

Directions

■ Do not take more than directed

■ children under 15 years: ask a doctor
■ adults and children 15 years and over: take 2 daytime capsules 2 times a day
■ Take 2 nighttime capsules before sleep
■ do not take nighttime capsule and daytime capsule together

INDICATIONS AND USAGE

temporarily relieves common cold and flu symptoms and minor aches

PACKAGE LABEL

NDC 69365-004-01

KEEP OUTER CARTON FOR COMPLETE WARNINGS AND PRODUCT INFORMATION
DO NOT TAKE DAY CAPSULE AND NIGHT CAPSULE TOGETHER

Facol Cold & Flu Day & Night

MULTI

Soft liquid filled capsule

Guaifenesin-expectorant

Acetaminophen-Fever/pain reliever

Phenylephrine HCl-Nasal Decongestant

Dextromethorphan HBr- Cough Suppressant

Diphenhydramine HCl-antihistamine (night time capsule only)

non drowsy Day

sleep aid Night

10 capsulesJW Pharmaceuticals